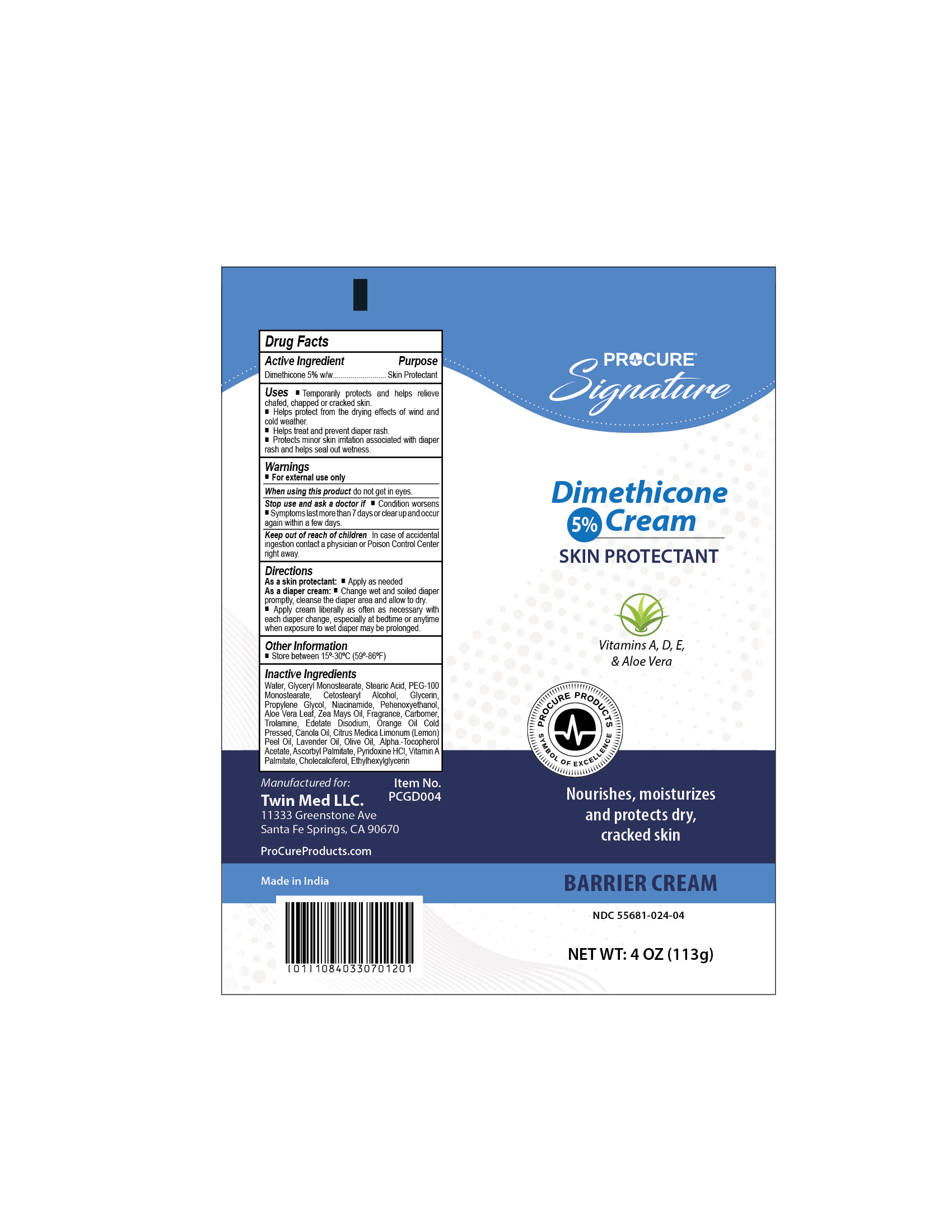 DRUG LABEL: Procure Dimethicone 5%
NDC: 55681-024 | Form: CREAM
Manufacturer: Twin Med LLC
Category: otc | Type: HUMAN OTC DRUG LABEL
Date: 20250628

ACTIVE INGREDIENTS: DIMETHICONE 5 g/100 g
INACTIVE INGREDIENTS: NIACINAMIDE; .ALPHA.-TOCOPHEROL ACETATE; ALOE VERA LEAF; ASCORBYL PALMITATE; CANOLA OIL; CARBOMER HOMOPOLYMER, UNSPECIFIED TYPE; CETOSTEARYL ALCOHOL; LEMON OIL, COLD PRESSED; EDETATE DISODIUM; ETHYLHEXYLGLYCERIN; GLYCERIN; GLYCERYL MONOSTEARATE; OLIVE OIL; ORANGE OIL, COLD PRESSED; PROPYLENE GLYCOL; TROLAMINE; VITAMIN A PALMITATE; WATER; ZEA MAYS (CORN) OIL; PYRIDOXINE HCL; PEG-100 MONOSTEARATE; STEARIC ACID; CHOLECALCIFEROL; LAVENDER OIL; PHENOXYETHANOL

Active Ingredient

Dimethicone 5%

Purpose

Skin Protectant

Uses

- temporaily protects and helps relieve chafed, chapped or cracked skin
- helps protect from the drying effects of whine and cold weather
- helps treat and prevent diaper rash
- protects minor skin irritation associated with diaper rash and helps seal out wetness

Warnings

For external use only

When using this product do not get into eyes.

Stop use and ask a doctor if

- condition worsens
- symptoms last more than 7 days or clear up and occur again within a few days

Keep out of reach of children. In case of accidental ingestion contact a physician or Poison Control Center right away.

Directions

As a skin protectant apply as needed

As a diaper cream

- change wet and soiled diaper promptly, cleanse the diaper area and allow to dry
- apply cream liberally as often as necessary with each diaper change, expecially at bedtime or anytime when exposure to wet diaper may be prolonged

Inactive Ingredients

Water, Glyceryl Monostearate, Stearic Acid, PEG-100 Monostearate, Cetostearyl Alcohol, Glycerin, Propylene Glycol, Niacinamide, Pehenoxyethanol, Aloe Vera Leaf, Zea Mays Oil, Fragrance, Carbomer, Trolamine, Edetate Disodium, Orange Oil Cold Pressed, Canola Oil, Citrus Medica Limonum (Lemon) Peel Oil, Lavender Oil, Olive Oil, .Alpha.-Tocopherol Acetate, Ascorbyl Palmitate, Pyridoxine HCl, Vitamin A Palmitate, Cholecalciferol, Ethylhexylglycerin